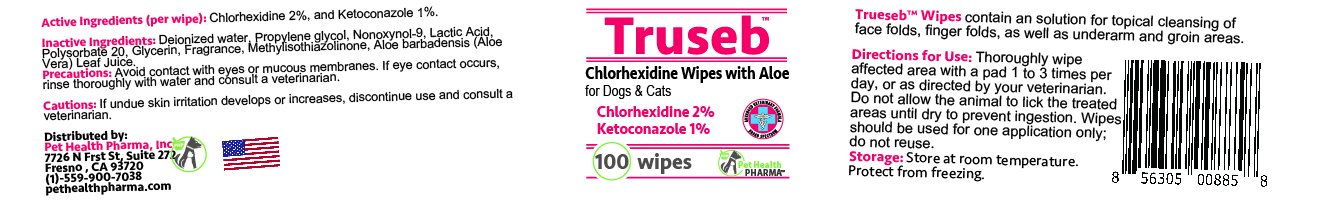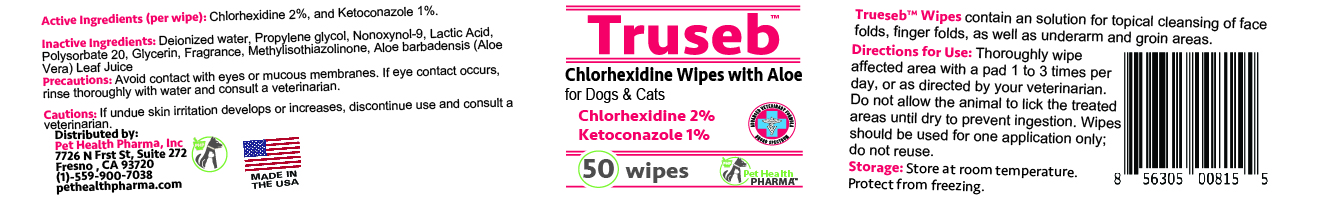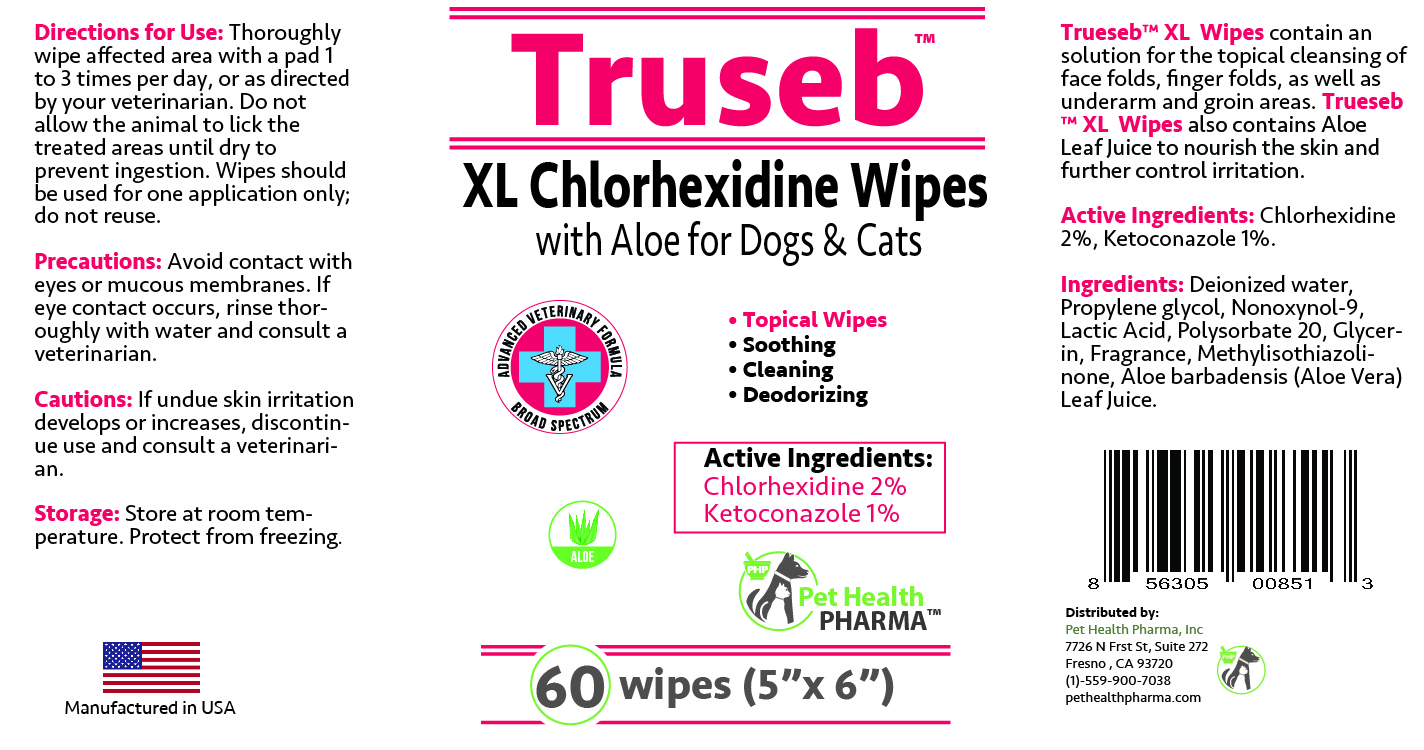 DRUG LABEL: TRUSEB CHLORHEXIDINE WITH ALOE FOR DOGS, CATS AND HORSES
NDC: 86176-204 | Form: CLOTH
Manufacturer: Pet Health Pharma, LLC
Category: animal | Type: OTC ANIMAL DRUG LABEL
Date: 20250214

ACTIVE INGREDIENTS: CHLORHEXIDINE GLUCONATE 20 mg/1 1; KETOCONAZOLE 10 mg/1 1
INACTIVE INGREDIENTS: WATER; PROPYLENE GLYCOL; NONOXYNOL-9; LACTIC ACID; POLYSORBATE 20; GLYCERIN; METHYLISOTHIAZOLINONE; ALOE VERA LEAF

TRUSEB CHLORHEXIDINE WITH ALOE FOR DOGS, CATS AND HORSES

Active Ingredients:

Chlorhexidine Gluconate 2% and Ketoconazole 1%

INACTIVE INGREDIENT:

Water, Propylene Glycol, Nonoxynol-9, Lactic Acid, Polysorbate 20, Glycerin, Fragrance, Methylisothiazolinone, Aloe Barbadensis (Aloe) Leaf Juice.

INDICATIONS & USAGE:

Trueseb™ Wipes contain an solution for the topical cleansing of face folds, finger folds, as well as underarm and groin areas.

DOSAGE & ADMINISTRATION:

Thoroughly wipe affected area with a pad 1 to 3 times per day, or as directed by your veterinarian. Do not allow the animal to lick the treated areas until dry to prevent ingestion. Wipes should be used for one application only; do not reuse.

PRECAUTIONS:

Avoid contact with eyes or mucous membranes. If eye contact occurs, rinse thoroughly with water and consult a veterinarian.

STORAGE AND HANDLING:

Store at controlled room temperature.

CAUTION:

If undue skin irritation develops or increases, discontinue use and consult a veterinarian.

SPL UNCLASSIFIED SECTION:

Chlorhexidine Wipes
with Aloe for Dogs & Cats

Topical Wipes

Deodorizing

Cleaning

Soothing

ADVANCED VETERINARY FORMULA
Broad Spectrum

MADE IN THE USA

Distributed by:
Pet Health Pharma, Inc
7726 N Frst St, Suite 272
Fresno , CA 93720
(1)-559-900-7038
pethealthpharma.com

PACKAGE LABEL

Packaging

Add image transcription here...

Add image transcription here...

Add image transcription here...